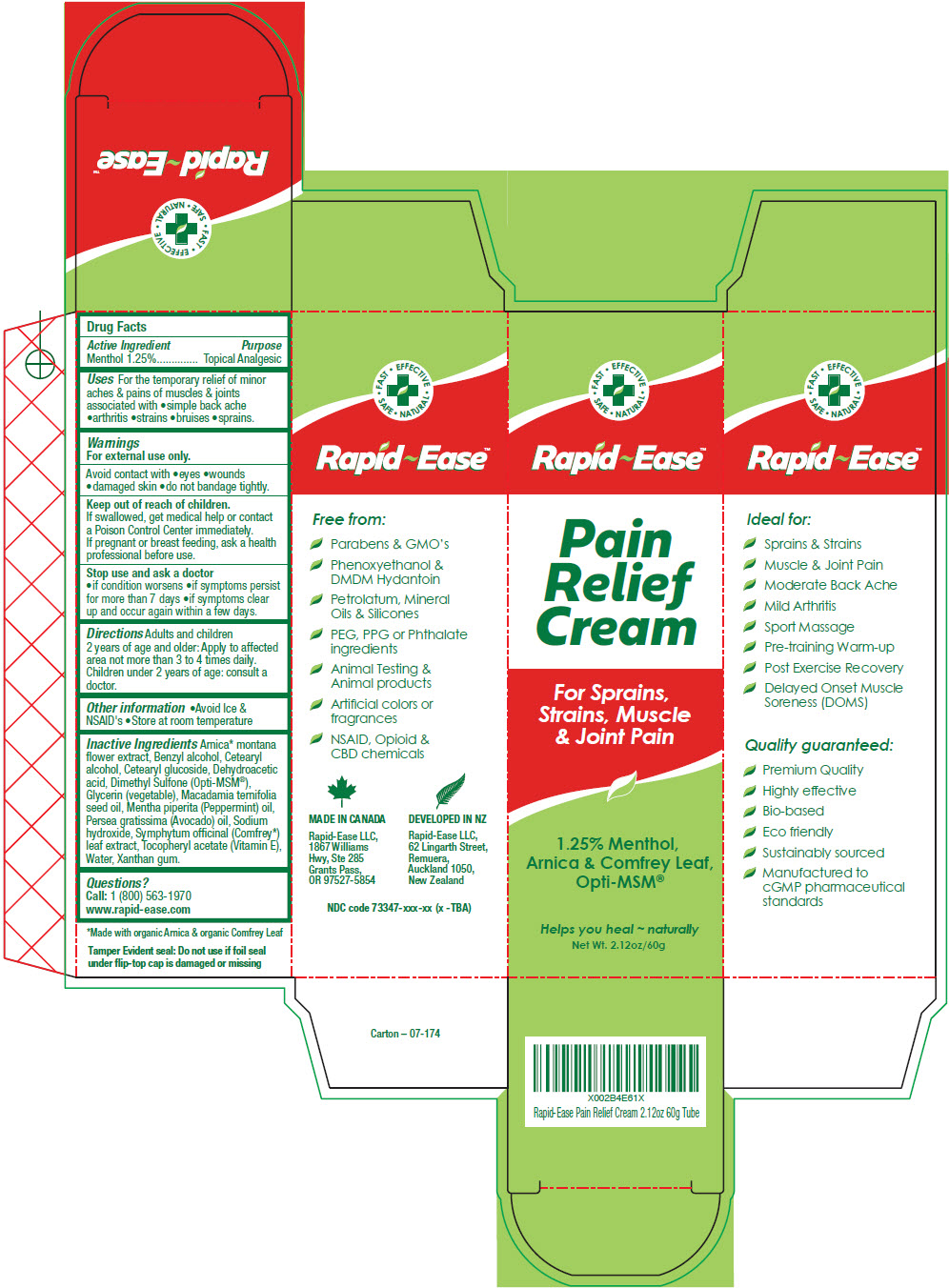 DRUG LABEL: Rapid-Ease Pain Relief 
NDC: 73347-117 | Form: CREAM
Manufacturer: Rapid-Ease
Category: otc | Type: HUMAN OTC DRUG LABEL
Date: 20190930

ACTIVE INGREDIENTS: Menthol, Unspecified Form 12.5 mg/1 g
INACTIVE INGREDIENTS: Arnica Montana Flower; Benzyl Alcohol; Cetostearyl Alcohol; CETEARYL GLUCOSIDE; Dehydroacetic Acid; Dimethyl Sulfone; Glycerin; Macadamia Oil; Peppermint Oil; Avocado Oil; Sodium Hydroxide; COMFREY LEAF; .ALPHA.-TOCOPHEROL ACETATE, DL-; Water; Xanthan Gum

Rapid-Ease™ Pain Relief Cream
Topical Analgesic

Drug Facts

Active Ingredient

Menthol 1.25%

Purpose

Topical Analgesic

Uses

For the temporary relief of minor aches & pains of muscles & joints associated with

- simple back ache
- arthritis
- strains
- bruises
- sprains.

Warnings

For external use only.

Avoid contact with

- eyes
- wounds
- damaged skin
- do not bandage tightly.

Keep out of reach of children.

If swallowed, get medical help or contact a Poison Control Center immediately.

If pregnant or breast feeding, ask a health professional before use.

Stop use and ask a doctor

- if condition worsens
- if symptoms persist for more than 7 days
- if symptoms clear up and occur again within a few days.

Directions

Adults and children 2 years of age and older: Apply to affected area not more than 3 to 4 times daily.

Children under 2 years of age: consult a doctor.

Other information

- Avoid Ice & NSAID's
- Store at room temperature

Inactive Ingredients

Arnica [Made with organic Arnica & organic Comfrey Leaf] montana flower extract, Benzyl alcohol, Cetearyl alcohol, Cetearyl glucoside, Dehydroacetic acid, Dimethyl Sulfone (Opti-MSM®), Glycerin (vegetable), Macadamia ternifolia seed oil, Mentha piperita (Peppermint) oil, Persea gratissima (Avocado) oil, Sodium hydroxide, Symphytum officinal (Comfrey) leaf extract, Tocopheryl acetate (Vitamin E), Water, Xanthan gum.

Questions?

Call: 1 (800) 563-1970

www.rapid-ease.com

PRINCIPAL DISPLAY PANEL - 60 g Tube Carton

• FAST • EFFECTIVE
• SAFE • NATURAL

Rapid~Ease™

Pain
Relief
Cream

For Sprains,
Strains, Muscle
& Joint Pain

1.25% Menthol,
Arnica & Comfrey Leaf,
Opti-MSM®

Helps you heal ~ naturally

Net Wt. 2.12oz/60g